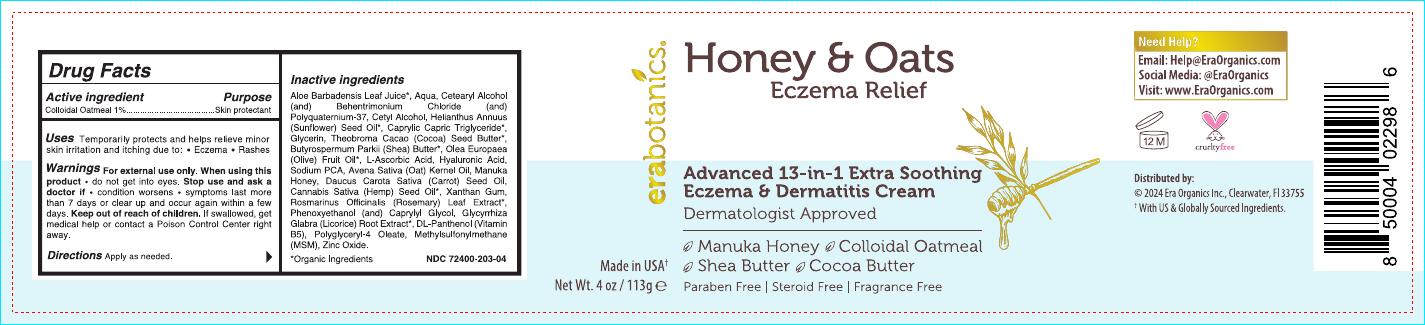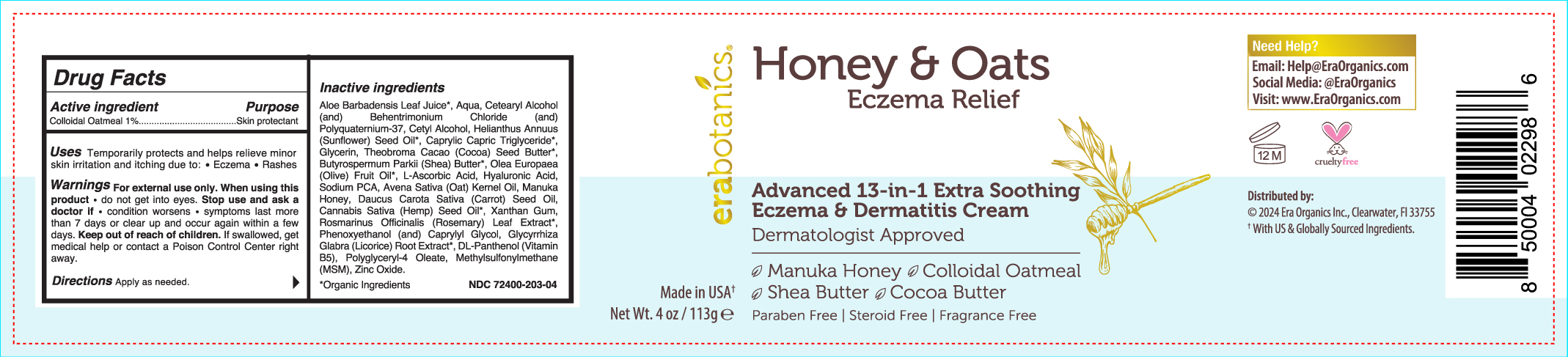 DRUG LABEL: Relief
NDC: 72400-203 | Form: CREAM
Manufacturer: Era Organics, Inc.
Category: otc | Type: HUMAN OTC DRUG LABEL
Date: 20251127

ACTIVE INGREDIENTS: OATMEAL 1.3 g/1.3 g

Relief - Advanced 13-in-1 Extra Soothing Eczema & Dermatitis Cream

Relief - Advanced 13-in-1 Extra Soothing Eczema & Dermatitis Cream

Aloe Barbadensis Leaf Juice*, Aqua, Cetearyl Alcohol (and) Behentrimonium Chloride (and) Polyquaternium-37, Cetyl Alcohol, Helianthus Annuus (Sunflower) Seed Oil, Caprylic/Capric Triglyceride*, Glycerin, Theobroma Cacao (Cocoa) Seed Butter*, Butyrospermum Parkii (Shea) Butter*, Cera Alba (Beeswax), Fruit Oil*, Ascorbic Acid, Sodium PCA, Anasataiva (Oat) Kernel Oil, Manuka Honey, Cocos Nucifera (Coconut) Oil, Avena Sativa (Oat) Kernel Extract, Xanthan Gum, Rosmarinus Officinalis (Rosemary) Leaf Extract*, Chamomilla Recutita (Matricaria) Extract, Glycyrrhiza Glabra (Licorice) Root Extract, DL-Panthenol (Vitamin B5), Polysorbate-4, Oleate, Methylsulfonylmethane (MSM), Zinc Oxide. (*Organic Ingredients)

Relief - Advanced 13-in-1 Extra Soothing Eczema & Dermatitis Cream

Colloidal Oatmeal 1%

Relief - Advanced 13-in-1 Extra Soothing Eczema & Dermatitis Cream

Skin protectant

Relief - Advanced 13-in-1 Extra Soothing Eczema & Dermatitis Cream

Keep out of reach of children. If swallowed, get medical help or contact a Poison Control Center right away.

Relief - Advanced 13-in-1 Extra Soothing Eczema & Dermatitis Cream

Stop use and ask a doctor if • condition worsens • symptoms last more than 7 days or clear up and occur again within a few days.

Relief - Advanced 13-in-1 Extra Soothing Eczema & Dermatitis Cream

Apply as needed. For external use only. When using this product • do not get into eyes

Relief - Advanced 13-in-1 Extra Soothing Eczema & Dermatitis Cream

Temporarily protects and helps relieve minor skin irritation and itching due to eczema and rashes.

Relief - Advanced 13-in-1 Extra Soothing Eczema & Dermatitis Cream

For external use only. When using this product - do not get into eyes.
Stop use and ask a doctor if condition worsens or symptoms last more than 7 days or clear up and occur again within a few days.